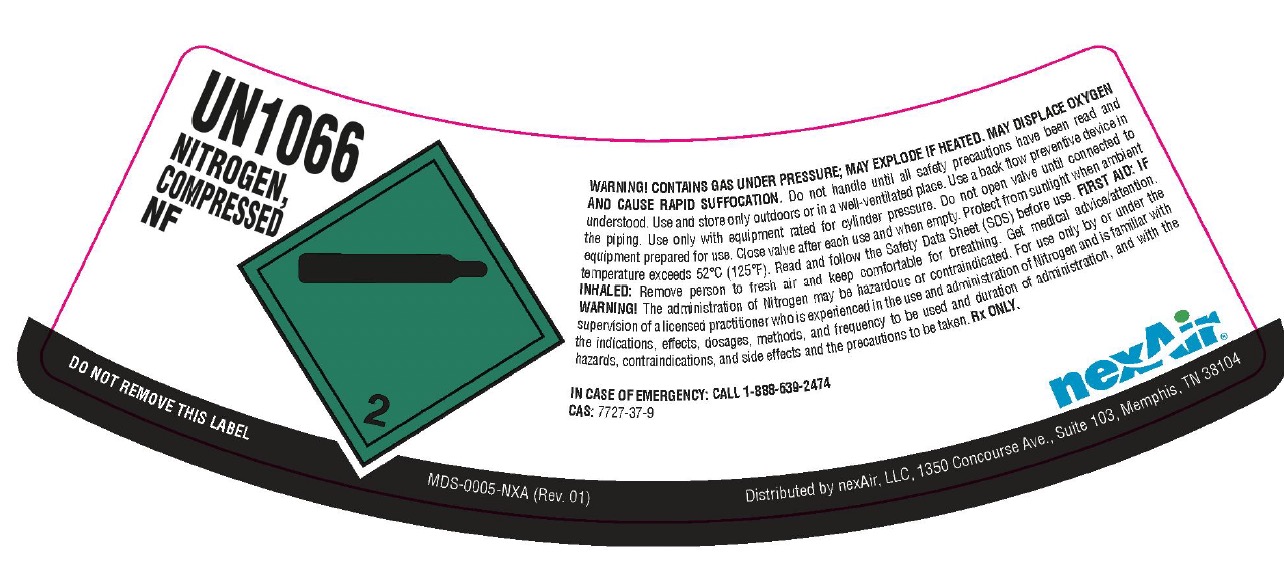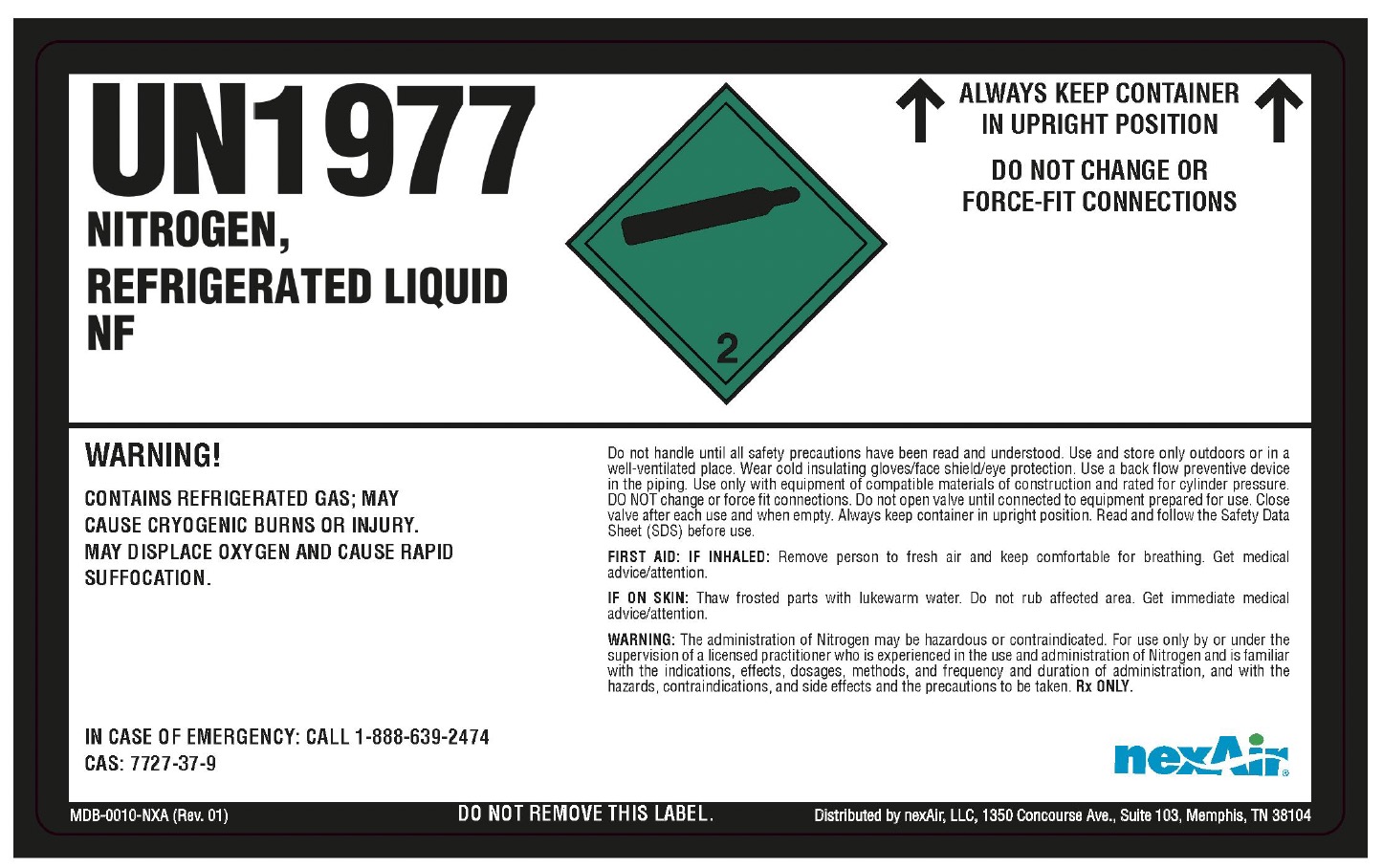 DRUG LABEL: Nitrogen
NDC: 33335-002 | Form: GAS
Manufacturer: WELSCO, INC.
Category: prescription | Type: HUMAN PRESCRIPTION DRUG LABEL
Date: 20251031

ACTIVE INGREDIENTS: NITROGEN 990 mL/1 L

Nitrogen

PACKAGE LABEL

UN1066

NITROGEN, COMPRESSED NF

DO NOT REMOVE THIS LABEL

WARNING! CONTAINS GAS UNDER PRESSURE; MAY EXPLODE IF HEATED. MAY DISPLACE OXYGEN AND CAUSE RAPID SUFFOCATION. Do not handle until all safety precautions have been read and understood. Use and store only outdoors or in a well-ventilated place. Use a back flow preventive device in the piping. Use only with equipment rated for cylinder pressure. Do not open valve until connected to equipment prepared for use. Close valve after each use and when empty. Protect from sunlight when ambient temperature exceeds 52 C (125 F). Read and follow the Safety Data Sheet (SDS) before use. FIRST AID: IF INHALED: Remove person to fresh air and keep comfortable for breathing. Get medical advice/attention. WARNING! The administration of Nitrogen may be hazardous or contraindicated. For use only by or under the supervision of a licensed practitioner who is experienced in the use and administration of Nitrogen and is familiar with the indications, effects, dosages, methods, and frequency to be used and duration of administration, and with the hazards, contraindications, and side effects and the precautions to be taken. Rx ONLY.

IN CASE OF EMERGENCY: CALL 1-888-639-2474

CAS: 7727-37-9

nexAir

Distributed by nexAir, LLC, 1350 Concourse Ave., Suite 103, Memphis, TN 38104

PACKAGE LABEL

UN1977

NITROGEN, REFRIGERATED LIQUID NF

WARNING!

CONTAINS REFRIGERATED GAS; MAY CAUSE CRYOGENIC BURNS OR INJURY. MAY DISPLACE OXYGEN AND CAUSE RAPID SUFFOCATION.

IN CASE OF EMERGENCY: CALL 1-888-639-2474

CAS: 7727-37-9

DO NOT REMOVE THIS LABEL.

ALWAYS KEEP CONTAINER IN UPRIGHT POSITION

DO NOT CHANGE OR FORCE-FIT CONNECTIONS

Do not handle until all safety precautions have been read and understood. Use and store only outdoors or in a well-ventilated place. Wear cold insulating gloves/face shield/eye protection. Use a back flow preventive device in the piping. Use only with equipment of compatible materials of construction and rated for cylinder pressure. DO NOT change or force fit connections. Do not open valve until connected to equipment prepared for use. Close valve after each use and when empty. Always keep container in upright position. Read and follow the Safety Data Sheet (SDS) before use.

FIRST AID: IF INHALED: Remove person to fresh air and keep comfortable for breathing. Get medical advice/attention.

IF ON SKIN: Thaw frosted parts with lukewarm water. Do not rub affected area. Get immediate medical advice/attention.

WARNING: The administration of Nitrogen may be hazardous or contraindicated. For use only by or under the supervision of a licensed practitioner who is experienced in the use and administration of Nitrogen and is familiar with the indications, effects, dosages, methods, and frequency to be used and duration of administration, and with the hazards, contraindications, and side effects and the precautions to be taken. Rx ONLY.

nexAir

Distributed by nexAir, LLC, 1350 Concourse Ave., Suite 103, Memphis, TN 38104